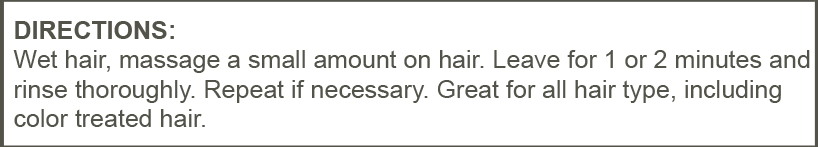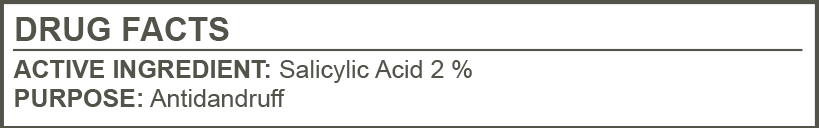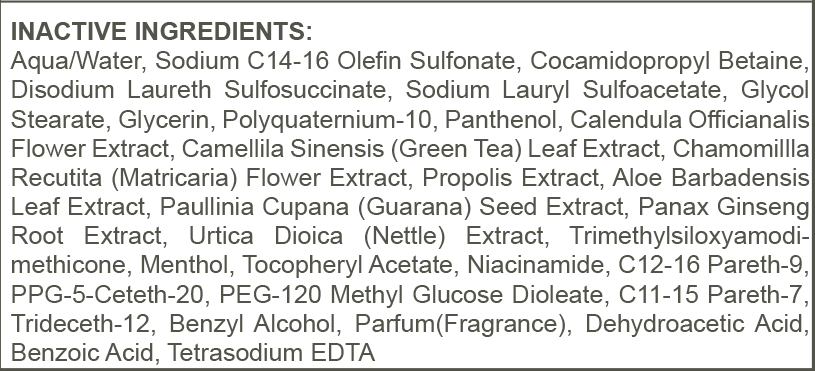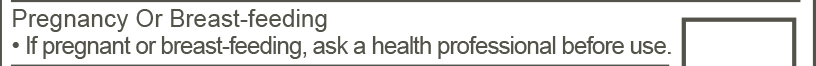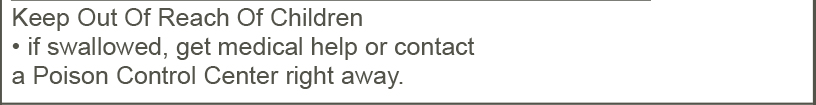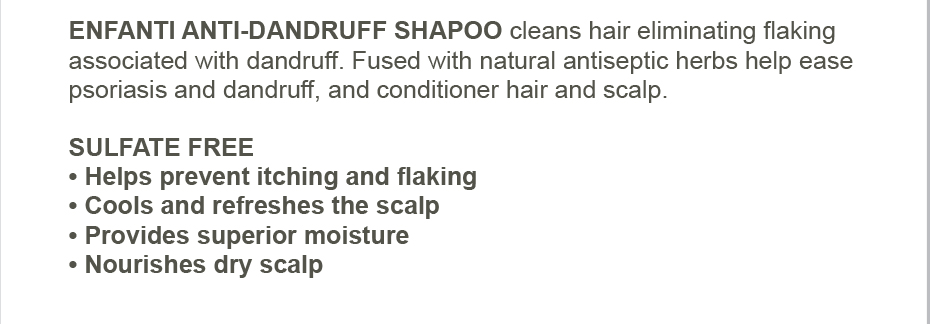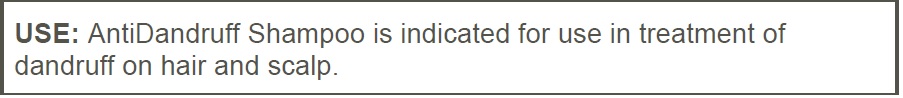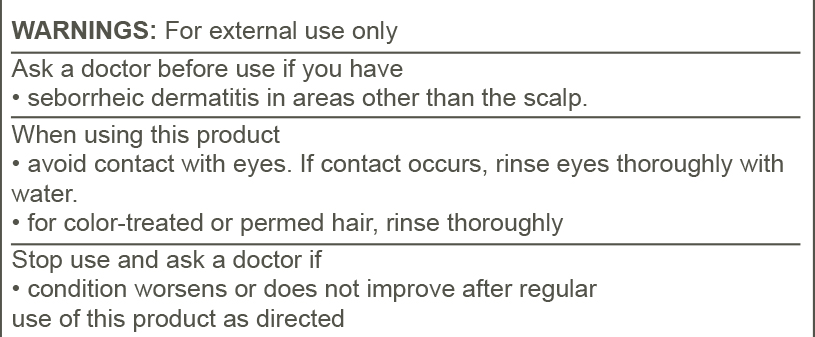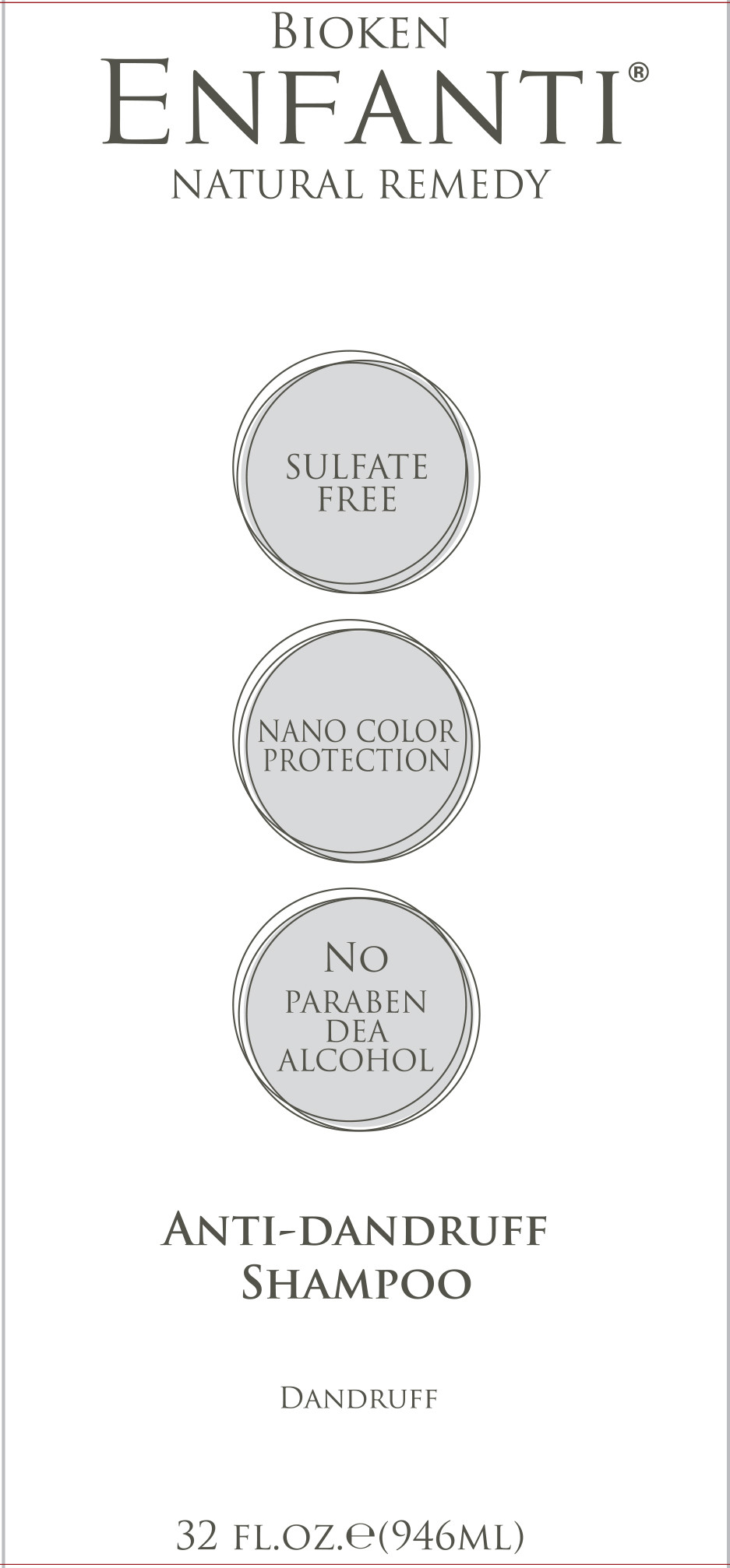 DRUG LABEL: Anti Dandruff
NDC: 71331-106 | Form: SHAMPOO
Manufacturer: Orange Lab
Category: otc | Type: HUMAN OTC DRUG LABEL
Date: 20230131

ACTIVE INGREDIENTS: SALICYLIC ACID 2 g/100 g
INACTIVE INGREDIENTS: EDETATE SODIUM TETRAHYDRATE; MENTHOL; C12-16 PARETH-9; DEHYDROACETIC ACID; TRIDECETH-12; MATRICARIA RECUTITA; COCAMIDOPROPYL BETAINE; WATER; ASIAN GINSENG; BENZYL ALCOHOL; SODIUM C14-16 OLEFIN SULFONATE; ALOE VERA LEAF; PEG-120 METHYL GLUCOSE DIOLEATE; ALPHA-TOCOPHEROL ACETATE; NIACINAMIDE; PPG-5-CETETH-20; SODIUM LAURYL SULFOACETATE; PROPOLIS WAX; URTICA DIOICA LEAF; GLYCERIN; PANTHENOL; POLYQUATERNIUM-10 (400 CPS AT 2%); CALENDULA OFFICINALIS FLOWER; DISODIUM LAURETH SULFOSUCCINATE; GLYCOL STEARATE; CAMELLIA SINENSIS WHOLE; PAULLINIA CUPANA SEED; BENZOIC ACID; C11-15 PARETH-7

Anti Dandruff Shampoo